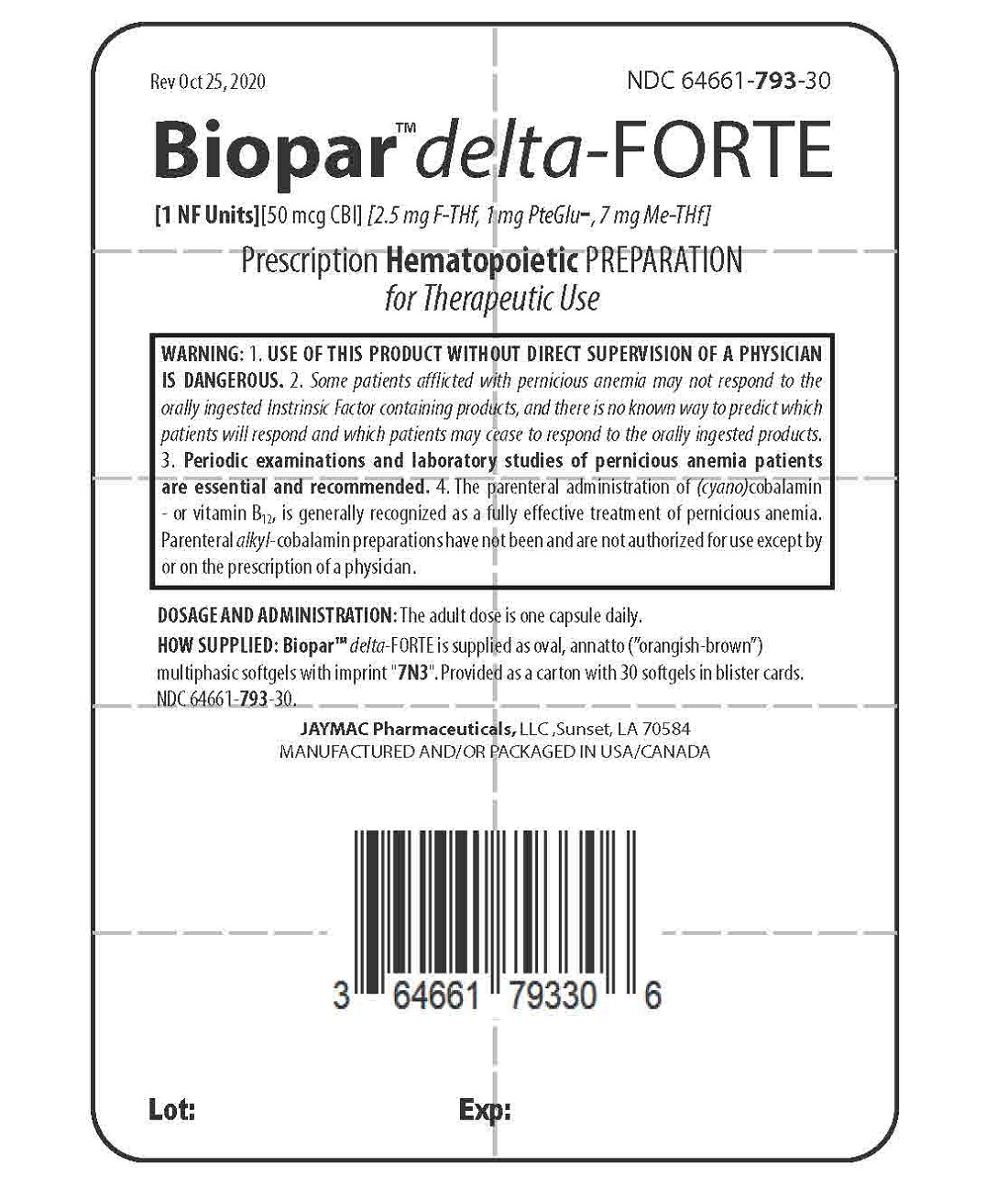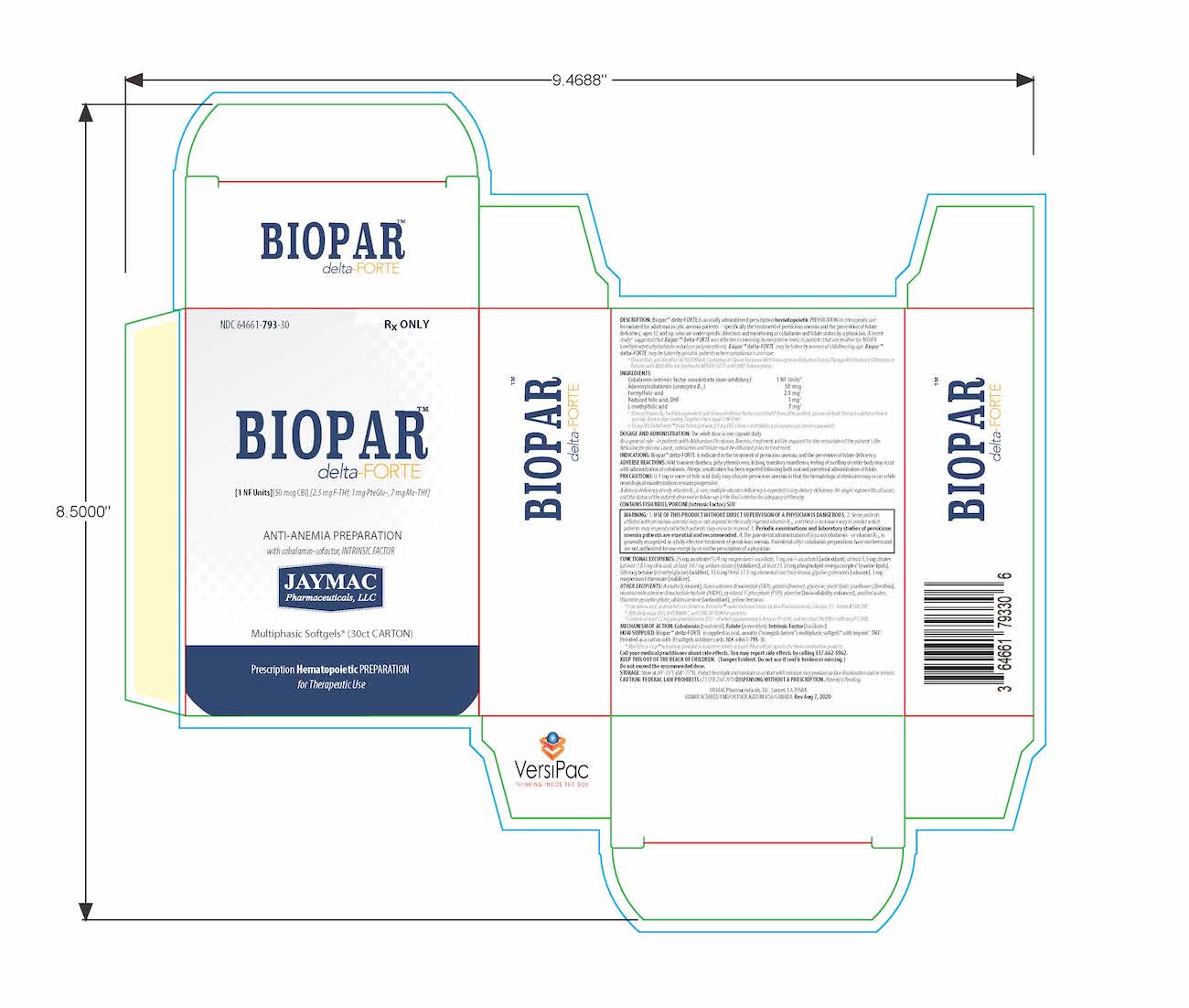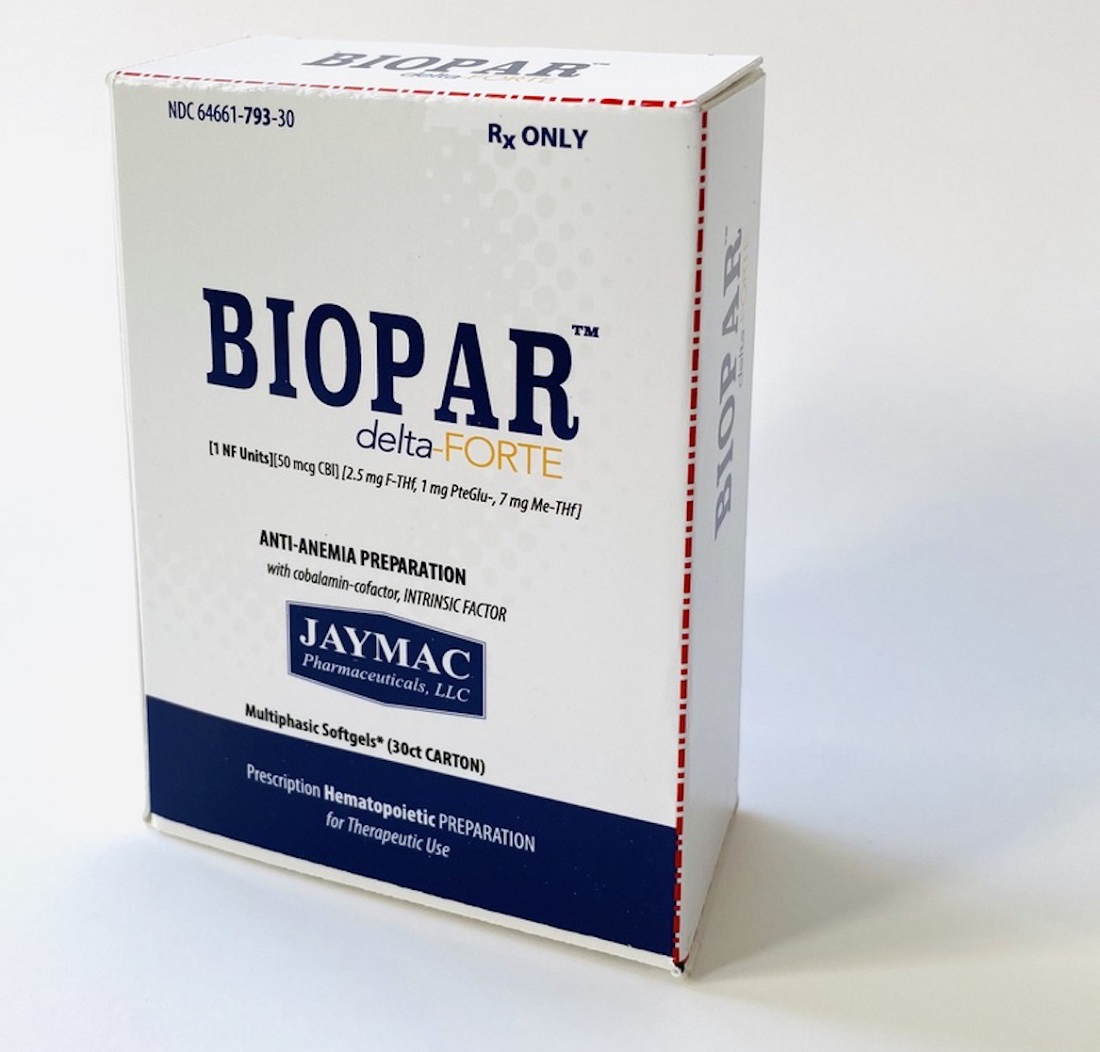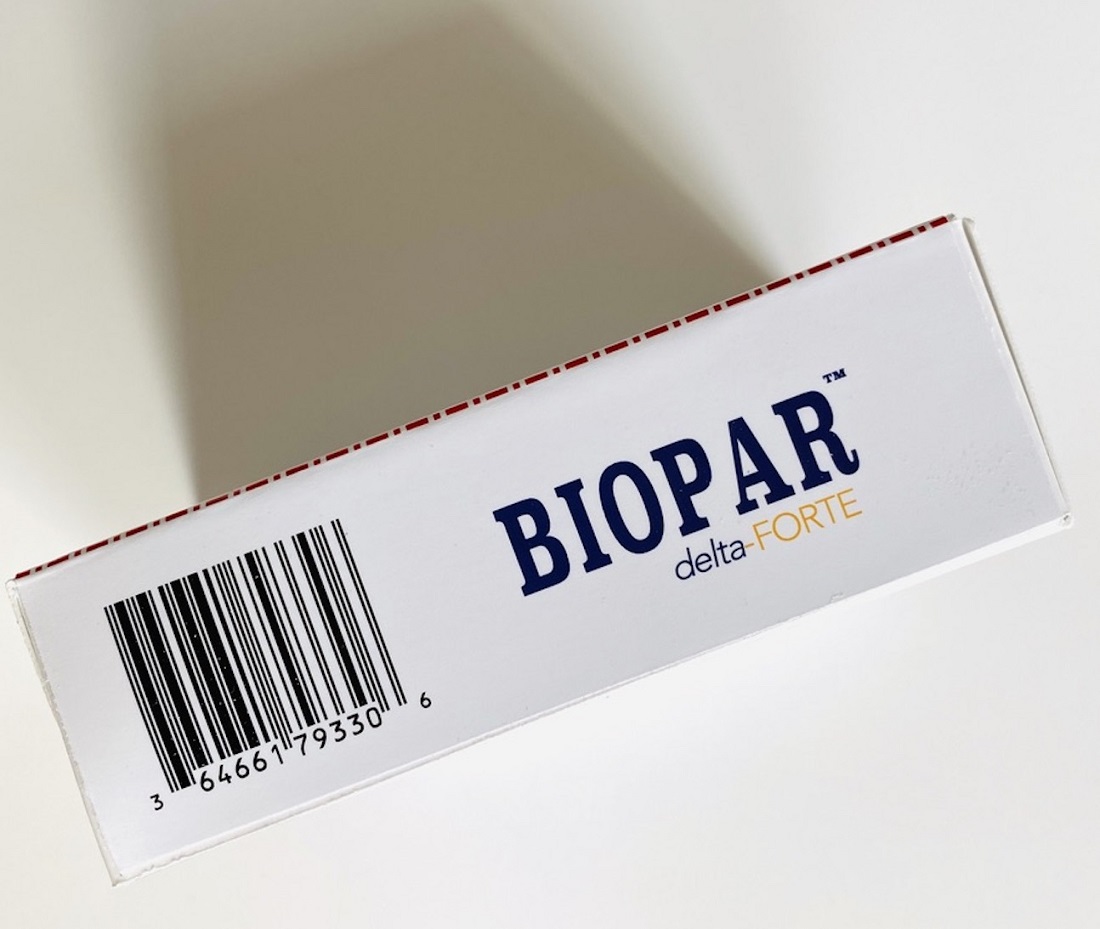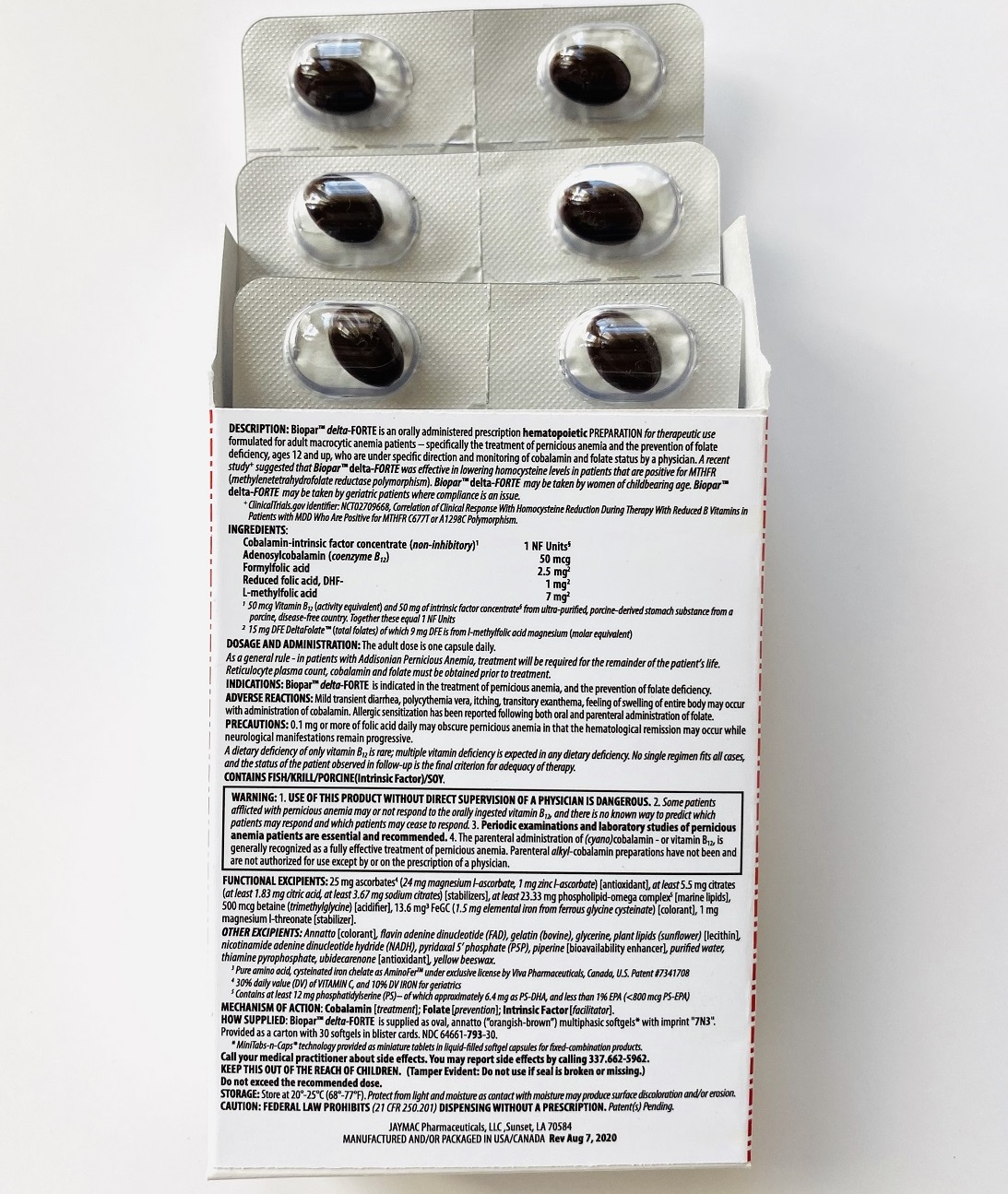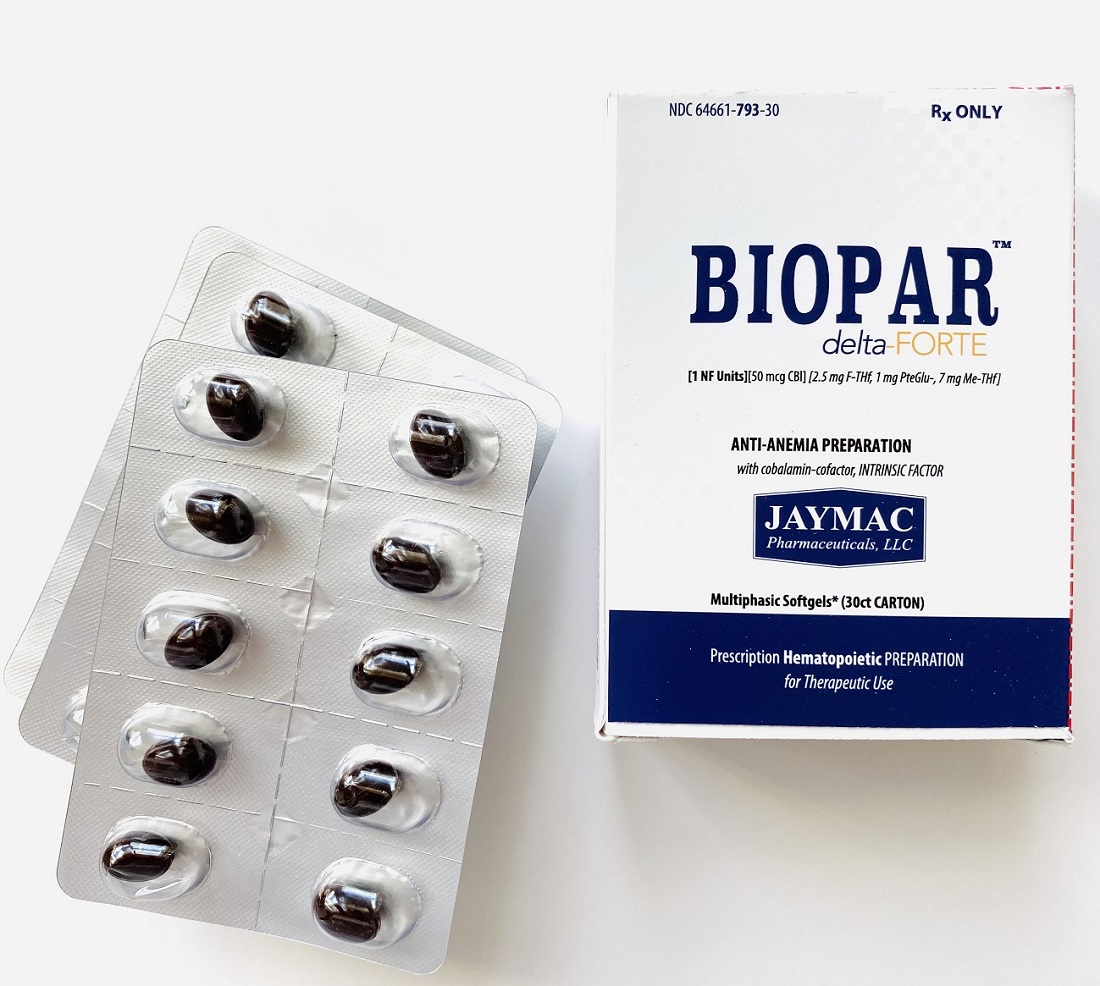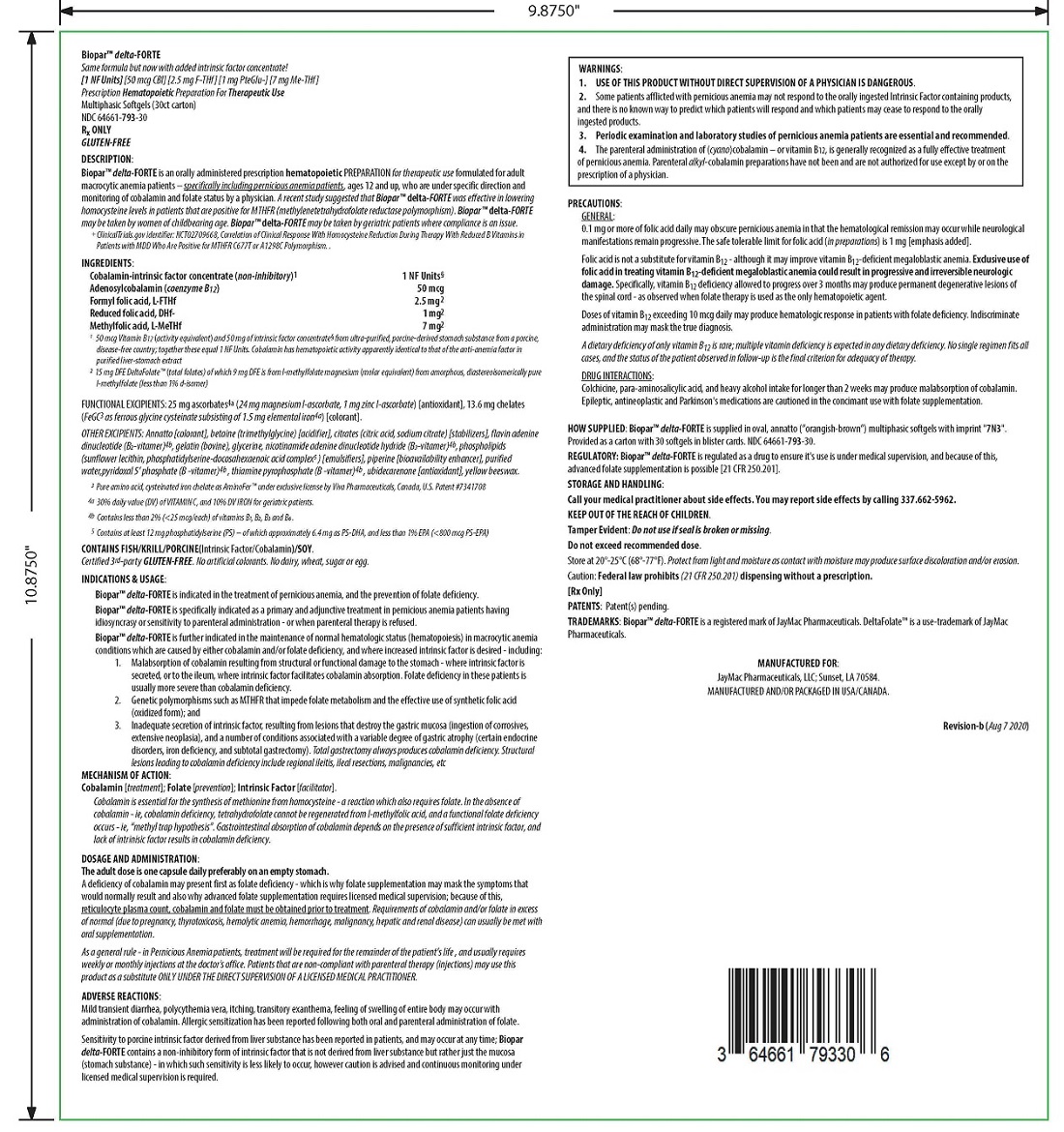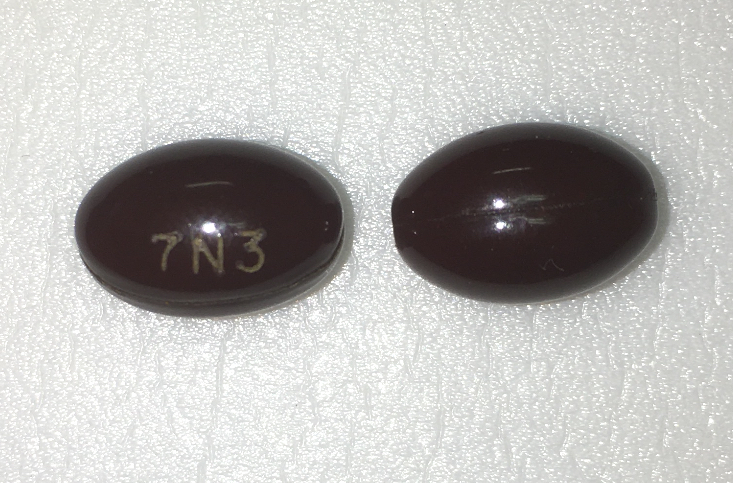 DRUG LABEL: Biopar delta-FORTE
NDC: 64661-793 | Form: CAPSULE
Manufacturer: Jaymac Pharma
Category: prescription | Type: HUMAN PRESCRIPTION DRUG LABEL
Date: 20251208

ACTIVE INGREDIENTS: INTRINSIC FACTOR 50 mg/1 1; COBALAMIN 50 ug/1 1; COBAMAMIDE 50 ug/1 1; levoLEUCOVORIN 2.5 mg/1 1; DIHYDROFOLIC ACID 1 mg/1 1; LEVOMEFOLATE MAGNESIUM 7 mg/1 1
INACTIVE INGREDIENTS: FERROUS CYSTEINE GLYCINATE 13.6 mg/1 1; 1,2-DOCOSAHEXANOYL-SN-GLYCERO-3-PHOSPHOSERINE CALCIUM 6.4 mg/1 1; 1,2-ICOSAPENTOYL-SN-GLYCERO-3-PHOSPHOSERINE CALCIUM 800 ug/1 1; PHOSPHATIDYL SERINE 12 mg/1 1; PYRIDOXAL PHOSPHATE ANHYDROUS 25 ug/1 1; FLAVIN ADENINE DINUCLEOTIDE 25 ug/1 1; NADH 25 ug/1 1; COCARBOXYLASE 25 ug/1 1; MAGNESIUM ASCORBATE 24 mg/1 1; ZINC ASCORBATE 1 mg/1 1; RIBOFLAVIN 5 mg/1 1; MAGNESIUM L-THREONATE 1 mg/1 1; BETAINE 500 ug/1 1; CITRIC ACID MONOHYDRATE 1.83 mg/1 1; SODIUM CITRATE 3.67 mg/1 1; ANNATTO; GELATIN, UNSPECIFIED; GLYCERIN; LECITHIN, SUNFLOWER; OLIVE OIL; PIPERINE; WATER; UBIDECARENONE; YELLOW WAX

BioparTM delta-FORTE

DESCRIPTION

[1 NF Units] [50 mcg CBl] [2.5 mg F-THf] [1 mg PteGlu-] [7 mg Me-THf]

Prescription Hematopoietic Preparation For Therapeutic Use

Multiphasic Softgels (30ct carton)

NDC 64661-793-30
Rx ONLY

BioparTM delta-FORTE is an orally administered prescription hematopoietic preparation for therapeutic use formulated for adult macrocytic anemia patients – specifically including pernicious anemia patients, ages 12 and up, who are under specific direction and monitoring of cobalamin and folate status by a physician.

INGREDIENTS

Cobalamin-intrinsic factor concentrate (non-inhibitory)^1 .............................................................................................. 1 NF Units§

Adenosylcobalamin (coenzyme B12) .............................................................................................................................. 50 mcg

Formyl folic acid, L-FTHf .............................................................................................................................................. 2.5 mg^2

Oxidized folic acid, DHf+ ................................................................................................................................................. 1 mg^2

Methyl folic acid, L-MeTHf ............................................................................................................................................... 7 mg^2

^1 50 mcg Vitamin B12 (activity equivalent) and 50 mg of intrinsic factor concentrate§ from ultra-purified, porcine-derived stomach substance from a porcine, disease-free country; together these equal 1 NF Units. Cobalamin has hematopoietic activity apparently identical to that of the anti-anemia factor in purified liver-stomach extract

^2 Total folates is from l-methylfolate magnesium (molar equivalent) from amorphous, diastereoisomerically pure l-methylfolate (less than 1% d-isomer), DHF-dependent provitamin B9 (folic acid included) and the levo-isomer of folinic acid (label claim molar equivalent).

INACTIVES

ALSO CONTAINS:

25 mg ascorbates4a (24 mg magnesium l-ascorbate, 1 mg zinc l-ascorbate) [antioxidant], 13.6 mg chelates (Cys-Fe^3 as cysteinated pure amino acid chelate subsisting of 1.5 mg elemental iron4a) [colorant], phospholipids (phosphatidylserine-docosahexaenoic acid complex^5)

OTHER INGREDIENTS:

Annatto [colorant], betaine (trimethylglycine) [acidifier], citrates (citric acid, sodium citrate) [stabilizers], flavin adenine dinucleotide (B2-vitamer)4b, gelatin (bovine), glycerine, nicotinamide adenine dinucleotide hydride (B3-vitamer)4b, phospholipids (sunflower lecithin) [emulsifiers], piperine [bioavailability enhancer], purified water, pyridoxal 5’ phosphate (B6-vitamer)4b, thiamine pyrophosphate (B1-vitamer)4b, ubidecarenone [antioxidant], yellow beeswax.

^3 Pure amino acid, cysteinated iron chelate.

4a 30% daily value (DV) of VITAMIN C, and 10% DV IRON for geriatric patients.

4b Contains less than 2% (<25 mcg/each) of vitamins B1, B2, B3 and B6.

^5 Contains at least 12 mg phosphatidylserine (PS) – of which approximately 6.4 mg as PS-DHA, and less than 1% EPA (<800 mcg PS-EPA)

CONTAINS

FISH/KRILL/PORCINE (Intrinsic Factor/Cobalamin)/SOY

Certified 3rd-party GLUTEN-FREE. No artificial colorants. No dairy, wheat, sugar or egg

INDICATIONS & USAGE

BioparTM delta-FORTE is specifically indicated as a primary and adjunctive treatment in pernicious anemia patients having idiosyncrasy or sensitivity to parenteral administration - or when parental therapy is refused;

MECHANISM OF ACTION

COBALAMIN [TREATMENT]; FOLATE [PREVENTION]; INTRINSIC FACTOR [B12-ADJUVENT] -

Cobalamin is essential for the synthesis of methionine from homocysteine - a reaction which also requires folate. In the absence of cobalamin - ie, cobalamin deficiency, tetrahydrofolate cannot be regenerated from l-methylfolic acid, and a functional folate deficiency occurs - ie, “methyl trap hypothesis”. Gastrointestinal absorption of cobalamin depends on the presence of sufficient intrinsic factor, and lack of intrinisic factor results in cobalamin deficiency.

DOSAGE & ADMINISTRATION

The adult dose is one capsule daily preferably on an empty stomach.

A deficiency of cobalamin may present first as folate deficiency - which is why folate supplementation may mask the symptoms that would normally result and also why advanced folate supplementation requires licensed medical supervision; because of this, reticulocyte plasma count, cobalamin and folate must be obtained prior to treatment. Requirements of cobalamin and/or folate in excess of normal (due to pregnancy, thyrotoxicosis, hemolytic anemia, hemorrhage, malignancy, hepatic and renal disease) can usually be met with oral supplementation.

As a general rule - in Pernicious Anemia patients, treatment will be required for the remainder of the patient’s life, and usually requires weekly or monthly injections at the doctor's office. Patients that are non-compliant with parenteral therapy (injections) may use this product as a substitute ONLY UNDER THE DIRECT SUPERVISION OF A LICENSED MEDICAL PRACTITIONER.

ADVERSE REACTIONS

Mild transient diarrhea, polycythemia vera, itching, transitory exanthema, feeling of swelling of entire body may occur with administration of cobalamin. Allergic sensitization has been reported following both oral and parenteral administration of folate.

Sensitivity to porcine intrinsic factor derived from liver substance has been reported in patients, and may occur at any time; BioparTM delta-FORTE contains a non-inhibitory form of intrinsic factor that is not derived from liver substance but rather just the mucosa (stomach substance) - in which such senstitivity is less likely to occur, however caution is advised and continuous monitoring under licensed medical supervision is required.

WARNING

USE OF THIS PRODUCT WITHOUT DIRECT SUPERVISION OF A PHYSICIAN IS DANGEROUS;
Some patients afflicted with pernicious anemia may or not respond to the orally ingested vitamin B12, and there is no known way to predict which patients may respond and which patients may cease to respond;
Periodic examinations and laboratory studies of pernicious anemia patients are essential and recommended; and -
The parenteral administration of (cyano)cobalamin - or vitamin B12, is generally recognized as a fully effective treatment of pernicious anemia. Parenteral alkyl-cobalamin preparations have not been and are not authorized for use except by or on the prescription of a physician.

PRECAUTIONS

GENERAL:

0.1 mg or more of folic acid daily may obscure pernicious anemia in that the hematological remission may occur while neurological manifestations remain progressive. The safe tolerable limit for folic acid (in preparations) is 1 mg [emphasis added];

Folic acid is not a substitute for vitamin B12 - although it may improve vitamin B12-deficient anemias. Exclusive use of folic acid in treating vitamin B12-deficient anemias could result in progressive and irreversible neurologic damage. Specifically, vitamin B12 deficiency allowed to progress over 3 months may produce permanent degenerative lesions of the spinal cord - as observed when folate therapy is used as the only hematopoietic agent;

Doses of vitamin B12 exceeding 10 mcg daily may produce hematologic response in patients with folate deficiency. Indiscriminate administration may mask the true diagnosis; and -

A dietary deficiency of only vitamin B12 is rare; multiple vitamin deficiency is expected in any dietary deficiency. No single regimen fits all cases, and the status of the patient observed in follow-up is the final criterion for adequacy of therapy.

DRUG INTERACTIONS:

Colchicine, para-aminosalicylic acid, and heavy alcohol intake for longer than 2 weeks may produce malabsorption of cobalamin.

Epileptic, antineoplastic and Parkinson's medications are cautioned in the concimant use with folate supplementation.

HOW SUPPLIED

BioparTM delta-FORTE is supplied as oval, annatto (”orangish-brown”) softgels* with imprint "7N3". Provided as a carton with 30 softgels in blister cards. NDC 64661-793-30.

REGULATORY

BioparTM delta-FORTE is regulated as a drug to ensure it's use is under medical supervision, and because of this, advanced folate supplementation is possible [21 CFR 250.201]. Intrinsic Factor was first marketed as Extralin(R) in 1932, and Extralin-B(R) with B-vitamins in 1936, followed by the Becotin(R) product which contained all the equivalent vitamins as this product plus intrinsic factor. "Old" drugs, including virtamins, which were considered safe prior to 1938, were permitted to continue on the market without further review. However, FDA maintained the authority to review these old drugs if possible safety concerns became apparent. In 1951, the Durham-Humphrey Act was passed. This act formally differentiated between prescription and OTC drugs. - 44 FR 16131 (March 16, 1979).

STORAGE AND HANDLING

Call your medical practitioner about side effects. You may report side effects by calling (337) 662-5962.

KEEP THIS OUT OF THE REACH OF CHILDREN.

(Tamper Evident: Do not use if seal is broken or missing)

Do not exceed the recommended dose.

STORAGE: Store at 20 ̊-25 ̊ C (68 ̊-77 ̊ F)

CAUTION: FEDERAL LAW PROHIBITS DISPENSING WITHOUT A PRESCRIPTION

[Rx ONLY]

PATENTS: Patent(s) pending.

TRADEMARKS: BioparTM delta-FORTEis a registered mark of JayMac Pharmaceuticals. DeltaFolateTM is a use-trademark of Jaymac Pharmaceuticals.

JAYMAC Pharmaceuticals, LLC

Sunset, LA 70584

MANUFACTURED AND/OR PACKAGED IN USA/CANADA

Revision

Dec 28, 2021